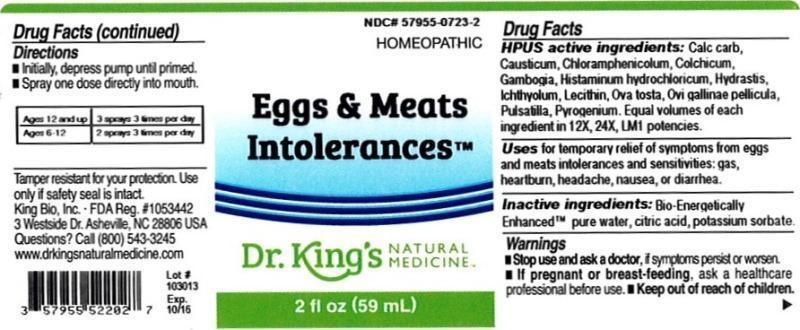 DRUG LABEL: Eggs and Meats Intolerances
NDC: 57955-0723 | Form: LIQUID
Manufacturer: King Bio Inc.
Category: homeopathic | Type: HUMAN OTC DRUG LABEL
Date: 20131119

ACTIVE INGREDIENTS: OYSTER SHELL CALCIUM CARBONATE, CRUDE 12 [hp_X]/59 mL; CAUSTICUM 12 [hp_X]/59 mL; CHLORAMPHENICOL 12 [hp_X]/59 mL; COLCHICUM AUTUMNALE BULB 12 [hp_X]/59 mL; GAMBOGE 12 [hp_X]/59 mL; HISTAMINE DIHYDROCHLORIDE 12 [hp_X]/59 mL; GOLDENSEAL 12 [hp_X]/59 mL; ICHTHAMMOL 12 [hp_X]/59 mL; EGG PHOSPHOLIPIDS 12 [hp_X]/59 mL; EGG SHELL, COOKED 12 [hp_X]/59 mL; EGG SHELL MEMBRANE 12 [hp_X]/59 mL; PULSATILLA VULGARIS 12 [hp_X]/59 mL; RANCID BEEF 12 [hp_X]/59 mL
INACTIVE INGREDIENTS: WATER; CITRIC ACID MONOHYDRATE; POTASSIUM SORBATE

Eggs and Meats Intolerances™

ACTIVE INGREDIENT

Drug Facts__________________________________________________________________________________________________________

HPUS active ingredients: Calcarea carbonica, Causticum, Chloramphenicolum, Colchicum autumnale, Gambogia, Histaminum hydrochloricum, Hydrastis canadensis, Ichthyolum, Lecithin, Ova tosta, Ovi gallinae pellicula, Pulsatilla, Pyrogenium. Equal volumes of each ingredient in 12X, 24X, LM1 potencies.

INDICATIONS AND USAGE

Uses for temporary relief of symptoms from eggs and meats intolerances and sensitivities: gas, heartburn, headache, nausea, or diarrhea.

Inactive Ingredients:

Bio-Energetically Enhanced™ pure water, citric acid and potassium sorbate.

Warnings

- Stop use and ask your doctor if symptoms persist or worsen.

- If pregnant or breast-feeding, ask a healthcare professional before use.

- Keep out of reach of children

DOSAGE AND ADMINISTRATION

- Initially, depress pump until primed.
- Spray one dose directly into mouth.
- Ages 12 and up- 3 sprays 3 times per day.
- Ages 6-12- 2 sprays 3 times per day.

OTHER SAFETY INFORMATION

Tamper resistant for your protection. Use only if safety seal is intact.

PURPOSE

Uses for temporary relief of symptoms from eggs and meats intolerances and sensitivities:

- gas
- heartburn
- headache
- nausea
- diarrhea